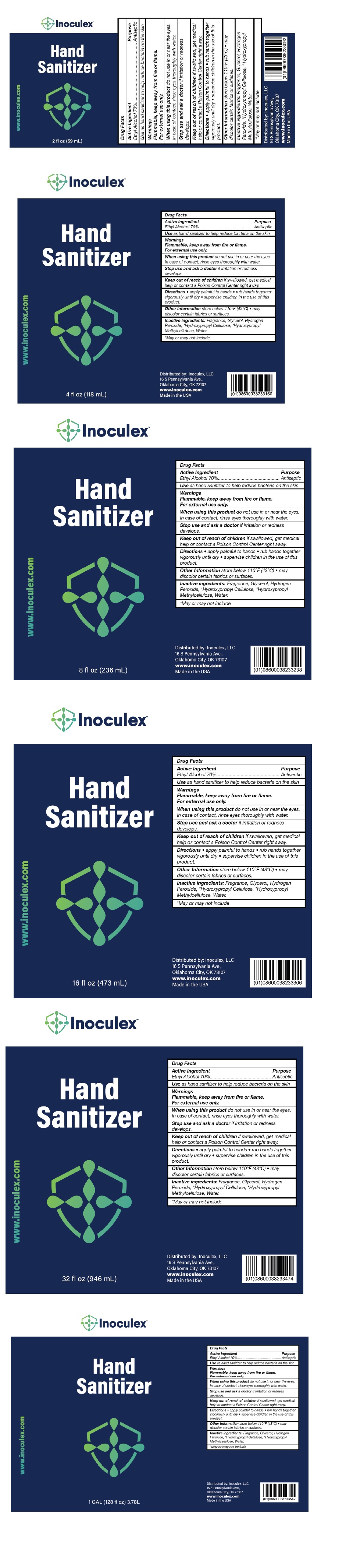 DRUG LABEL: Inoculex Hand Sanitizer
NDC: 77017-015 | Form: LIQUID
Manufacturer: Private Label Supplements
Category: otc | Type: HUMAN OTC DRUG LABEL
Date: 20200504

ACTIVE INGREDIENTS: ALCOHOL 70 mL/100 mL
INACTIVE INGREDIENTS: GLYCERIN; HYDROGEN PEROXIDE; HYDROXYPROPYL CELLULOSE, UNSPECIFIED; HYPROMELLOSE, UNSPECIFIED; WATER

InoculexTM Hand Sanitizer

Active Ingredient

Ethyl Alcohol 70%

Purpose

Antiseptic

INDICATIONS AND USAGE

Use as hand sanitizer to help reduce bacteria on the skin

Warnings

Flammable, keep away from fire or flame.

For external use only.

When using this product do not use in or near the eyes. In case of contact, rinse eyes thoroughly with water.

Stop use and ask a doctor if irritation or redness develops.

Keep out of reach of children if swallowed, get medical help or contact a Poison Control Center right away.

DOSAGE AND ADMINISTRATION

Directions • apply palmful to hands • rub hands together vigorously until dry • supervise children in the use of this product.

Other Information store below 110°F (43°C) • may discolor certain fabrics or surfaces.

INACTIVE INGREDIENT

Inactive ingredients: Fragrance, Glycerol, Hydrogen Peroxide, *Hydroxypropyl Cellulose, *Hydroxypropyl Methycellulose, Water

*May or may not include

www.inoculex.com

Distributed by: Inoculex, LLC

16 S Pennsylvania Ave.,

Oklahoma City, OK 73107

Made in the USA